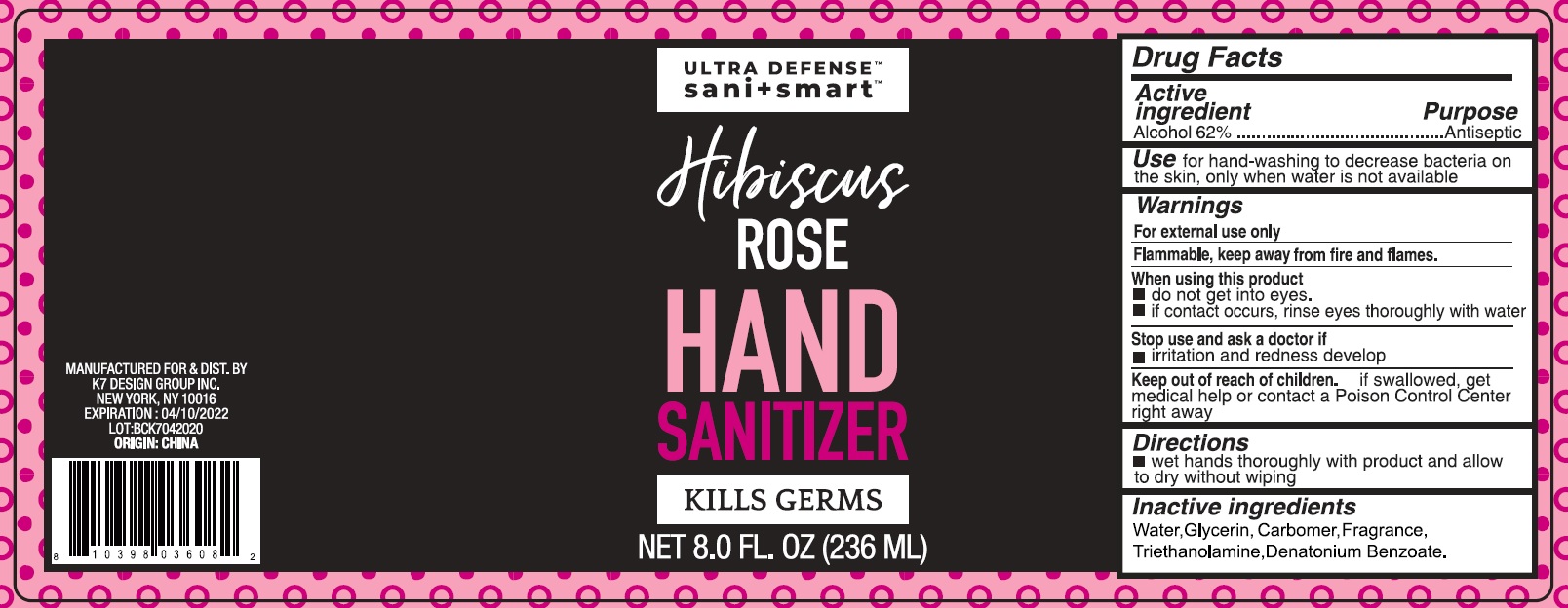 DRUG LABEL: Hibiscus ROSE HAND SANITIZER
NDC: 74177-024 | Form: GEL
Manufacturer: K7 Design Group Inc.
Category: otc | Type: HUMAN OTC DRUG LABEL
Date: 20231026

ACTIVE INGREDIENTS: ALCOHOL 0.62 mL/1 mL
INACTIVE INGREDIENTS: WATER; GLYCERIN; CARBOXYPOLYMETHYLENE; TROLAMINE; DENATONIUM BENZOATE

Hibiscus ROSE HAND SANITIZER

Active ingredient

Alcohol 62%

Purpose

Antiseptic

Use

for hand-washing to decrease bacteria on the skin, only when water is not available

Warnings

For external use only

Flammable, keep away from fire or flames.

When using this product

- do not get into eyes.
- if contact occurs, rinse eyes thoroughly with water

Stop use and ask a doctor if

- Irritation and redness develop

Keep out of reach of children.

If swallowed, get medical help or contact a Poison Control Center right away.

Directions

- wet hands thoroughly with product and allow to dry without wiping

Inactive ingredients

Water, Glycerin, Carbomer, Fragrance, Triethanolamine, Denatonium Benzoate.